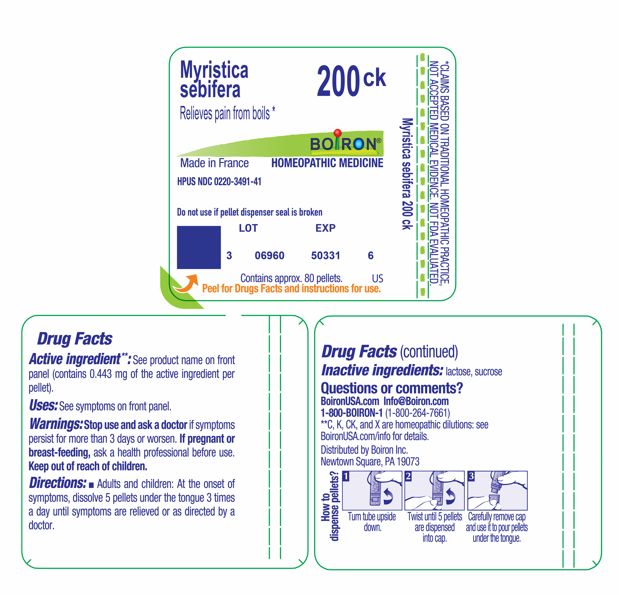 DRUG LABEL: MYRISTICA SEBIFERA
NDC: 0220-3491 | Form: PELLET
Manufacturer: Boiron
Category: homeopathic | Type: HUMAN OTC DRUG LABEL
Date: 20260122

ACTIVE INGREDIENTS: VIROLA SEBIFERA RESIN 200 [kp_C]/200 [kp_C]
INACTIVE INGREDIENTS: SUCROSE; LACTOSE, UNSPECIFIED FORM

MYRISTICA SEBIFERA 200CK MD

ACTIVE INGREDIENT

Myristica sebifera 200CK HPUS

Active ingredient**: See product name on front panel (contains 0.443 mg of the active ingredient per pellet).

Purpose*

INDICATIONS AND USAGE

Relieves pain from boils *

Warnings

Stop use and ask a doctor if symptoms persist for more than 3 days or worsen.

PREGNANCY OR BREAST FEEDING

If pregnant or breast-feeding, ask a health professional before use.

Keep out of reach of children.

DOSAGE AND ADMINISTRATION

Adults and children: At the onset of symptoms, dissolve 5 pellets under the tongue 3 times a day until symptoms are relieved or as directed by a doctor.

INACTIVE INGREDIENT

lactose, sucrose

QUESTIONS

BoironUSA.com Info@boiron.com
1-800-BOIRON-1 (1-800-264-7661)
Distributed by Boiron, Inc.
Newtown Square, PA 19073

Do not use if pellet dispenser seal is broken.
Contains approx 80 pellets.
How to dispense pellets? Turn tube upside down. Twist until 5 pellets are dispensed into cap. Carefully remove the cap and use it to pour pellets under the tongue.
*CLAIMS BASED ON TRADITIONAL HOMEOPATHIC PRACTICE NOT ACCEPTED MEDICAL EVIDENCE. NOT FDA EVALUATED.
*C,K,CK, and X are homeopathic dilutions: see BoironUSA.com/info for details.